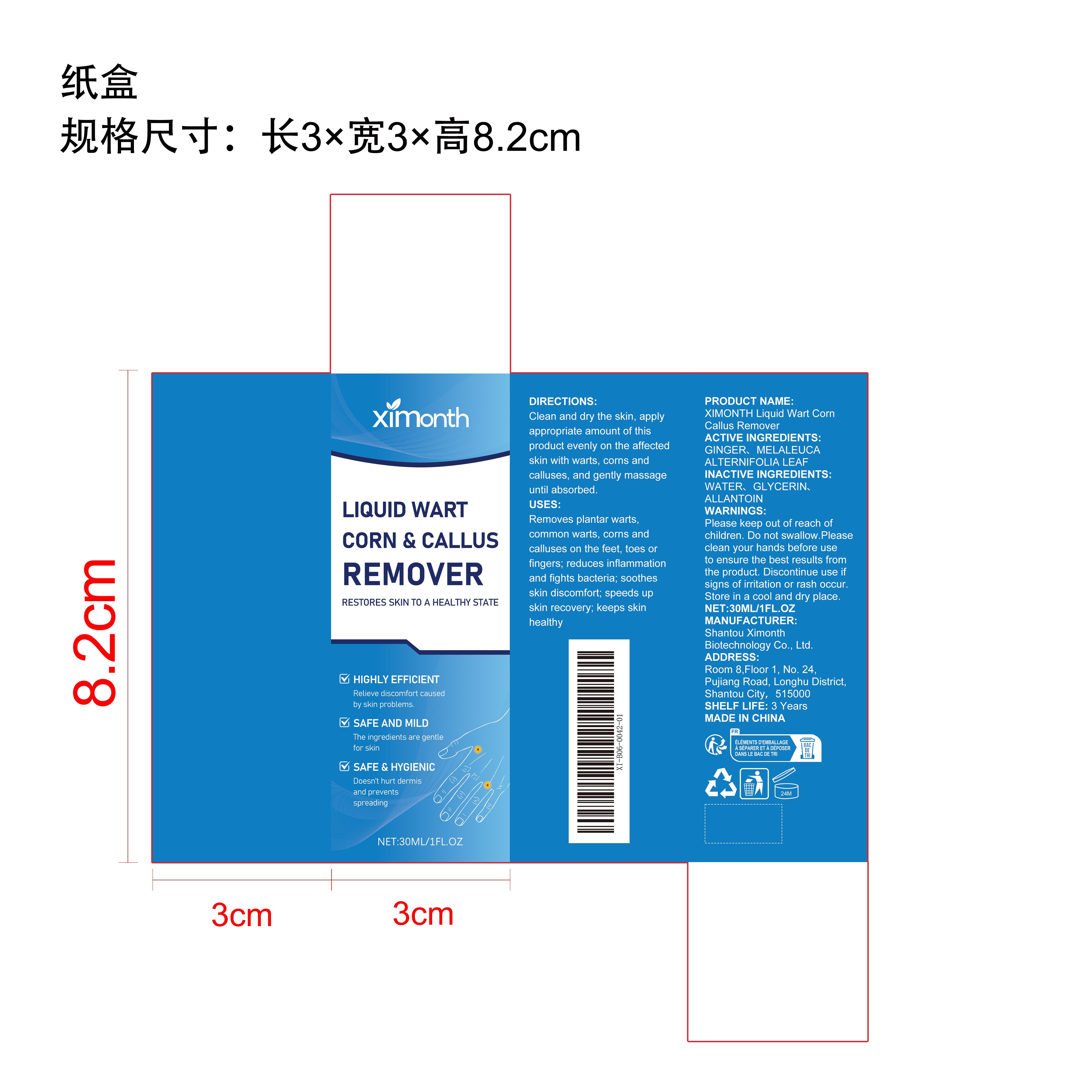 DRUG LABEL: XIMONTH Liquid Wart Corn Callus Remover
NDC: 84989-007 | Form: LIQUID
Manufacturer: Shantou Ximonth Biotechnology Co., Ltd.
Category: otc | Type: HUMAN OTC DRUG LABEL
Date: 20251126

ACTIVE INGREDIENTS: MELALEUCA ALTERNIFOLIA LEAF 0.006 mg/30 mg; GINGER 0.006 mg/30 mg
INACTIVE INGREDIENTS: ALLANTOIN 0.006 mg/30 mg; WATER 27.582 mg/30 mg; GLYCERIN 2.4 mg/30 mg

ACTIVE INGREDIENT

GINGER、MELALEUCA ALTERNIFOLIA LEAF

WHEN USING

Clean and dry the skin, apply appropriate amount of this product evenly on the affected skin with warts, corns and calluses, and gently massage until absorbed.

WARNINGS

Please keep out of reach of children. Do not swallow.Please clean your hands before use to ensure the best results from the product. Discontinue use if signs of irritation or rash occur. Store in a cool and dry place.

PURPOSE

Removes plantar warts, common warts, corns and calluses on the feet, toes or fingers; reduces inflammation and fights bacteria; soothes skin discomfort; speeds up skin recovery; keeps skin healthy

DO NOT USE

Discontinue use if signs of irritation or rash occur.

STOP USE

Discontinue use if signs of irritation or rash occur.

KEEP OUT OF REACH OF CHILDREN

Please keep out of reach of children. Do not swallow.

STORAGE AND HANDLING

Store in a cool and dry place.

INACTIVE INGREDIENT

WATER、GLYCERIN、ALLANTOIN